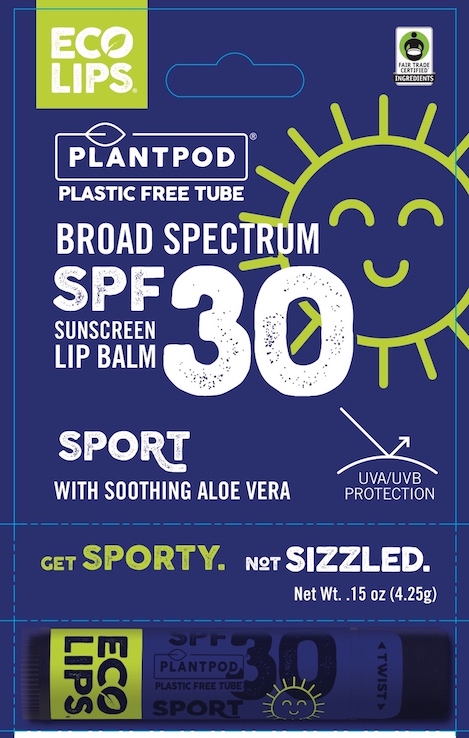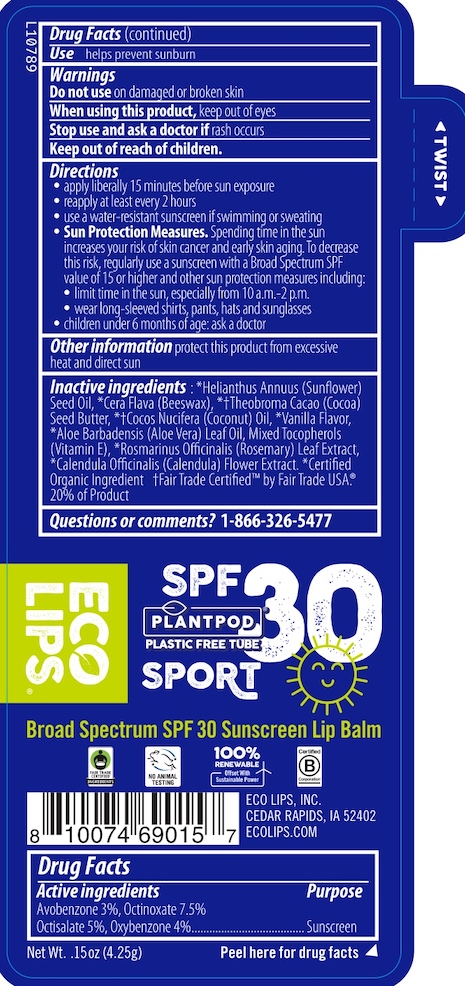 DRUG LABEL: Eco Lips PlantPod Sunscreen Lip Balm Sport
NDC: 75071-007 | Form: STICK
Manufacturer: Eco Lips. Inc.
Category: otc | Type: HUMAN OTC DRUG LABEL
Date: 20240722

ACTIVE INGREDIENTS: OCTINOXATE 7.5 g/100 g; OXYBENZONE 4 g/100 g; AVOBENZONE 3 g/100 g; OCTISALATE 5 g/100 g
INACTIVE INGREDIENTS: ROSEMARY OIL; ALOE VERA LEAF; CALENDULA OFFICINALIS FLOWER; YELLOW WAX; SUNFLOWER OIL; COCOA BUTTER; TOCOPHEROL; COCONUT OIL

01015 - 01127 Eco Lips Plant Pod Lip Balm Sport SPF 30

Drug Facts

Active ingredients

Avobenzone 3%, Octinoxate 7.5%, Octisalate 5%, Oxybenzone 4%

Purpose

Sunscreen

Use

helps prevent sunburn

Warnings

Do not use on damaged or broken skin

When using this product keep out of eyes

Stop use and ask a doctor if rash occurs

Keep out of reach of children.

Directions

- apply liberally 15 minutes before sun exposure
- reapply at least every 2 hours
- use a water-resistant sunscreen if swimming or sweating
- Sun Protection Measures. Spending time in the sun increases your risk of skin cancer and early skin aging. To decrease this risk, regularly use a sunscreen with a Broad Spectrum SPF value of 15 or higher and other sun protection measures including:
- limit time in the sun, especially from 10 a.m. - 2 p.m.
- wear long-sleeved shirts, pants, hats and sunglasses
- children under 6 months of age: ask a doctor

Other information

protect this product from excessive heat and direct sun

Inactive ingredients

*Helianthus Annuus (Sunflower) Seed Oil, *Cera Flava (Beeswax), *†Theobroma Cacao (Cocoa) Seed Butter, *†Cocos Nucifera (Coconut) Oil, *Vanilla Flavor, *Aloe Barbadensis (Aloe Vera) Leaf Oil, Mixed Tocopherols (Vitamin E), *Rosmarinus Officinalis (Rosemary) Leaf Extract, *Calendula Officinalis (Calendula) Flower Extract.

* Certified Organic Ingredient † Fair Trade Certified™ by Fair Trade USA®. 20% of Product.

Questions or comments?

1-866-326-5477

ECO LIPS, INC. | CEDAR RAPIDS, IA 52402

ECOLIPS.COM

MANUFACTURED IN USA

INDIVIDUAL TUBE LABEL

ECO LIPS®

SPF 30

PLANTPOD SPORT

Broad Spectrum SPF 30 Sunscreen Lip Balm

Net Wt.. .15oz (4.25g)

BLISTER PACK CARTON PDP

ECO LIPS®

PLANTPOD

BROAD SPECTRUM SPF 30 SUNSCREEN LIP BALM

SPORT

WITH SOOTHING ALOE VERA

UVA/UVB PROTECTIO

Net Wt. .15 oz (4.25g)